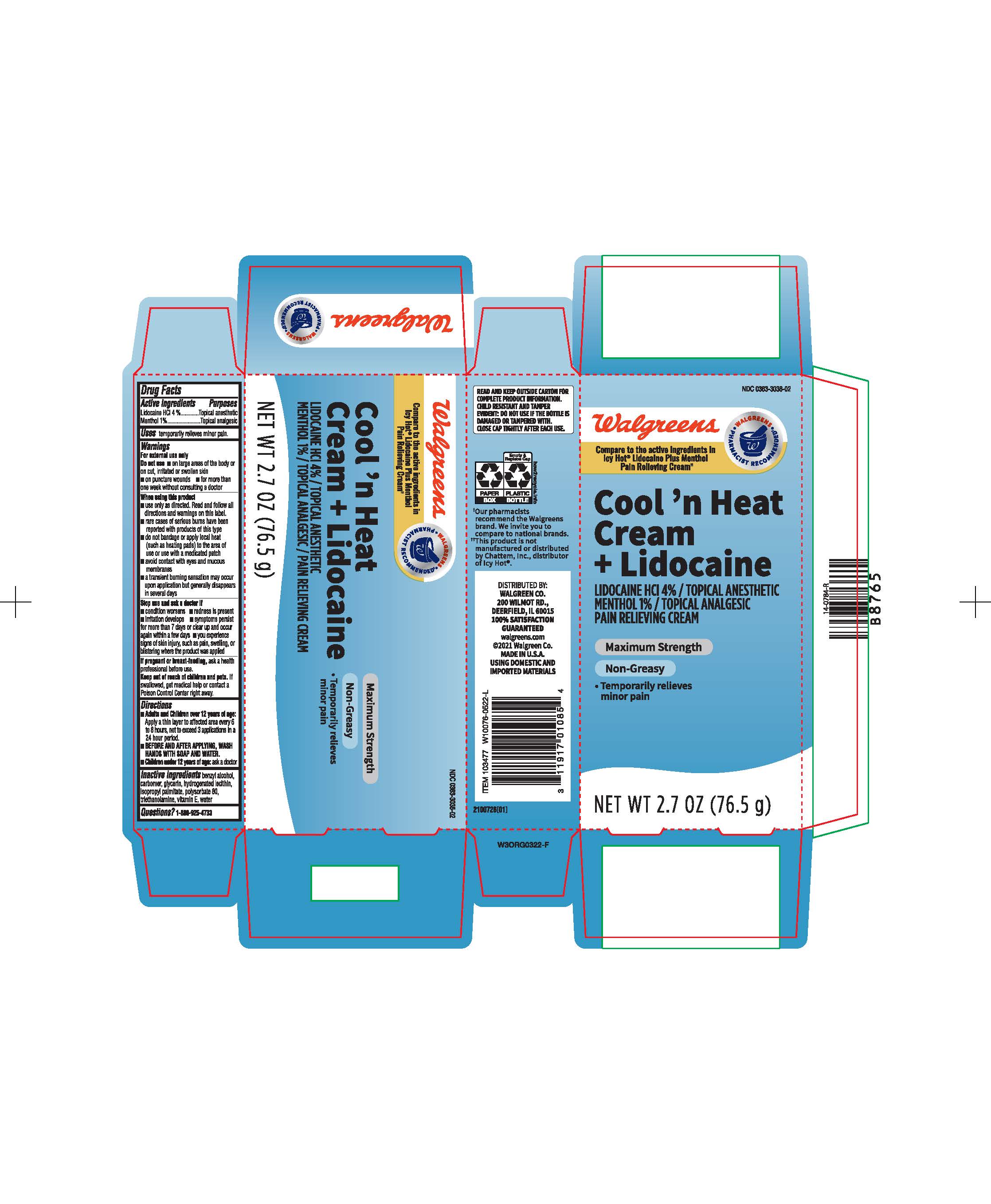 DRUG LABEL: Walgreens Cool n Heat
NDC: 0363-3036 | Form: CREAM
Manufacturer: Walgreens
Category: otc | Type: HUMAN OTC DRUG LABEL
Date: 20241211

ACTIVE INGREDIENTS: MENTHOL, UNSPECIFIED FORM 1 g/100 g; LIDOCAINE HYDROCHLORIDE 4 g/100 g
INACTIVE INGREDIENTS: WATER; POLYSORBATE 80; GLYCERIN; BENZYL ALCOHOL; TOCOPHEROL; ISOPROPYL PALMITATE; TROLAMINE; HYDROGENATED SOYBEAN LECITHIN

Walgreen cool n heat cream with lidocaine

ACTIVE INGREDIENT

Lidocaine HCL 4%

Menthol 1%

PURPOSE

Topical anesthetic

Topical anagesic

INDICATIONS AND USAGE

Temporarily relieves minor pain

DOSAGE AND ADMINISTRATION

- Adults and children over 12 years of age: Apply a thin layer to the affected area every 6 to 8 hours, not exceeding 3 applications in a 24 hr period.
- Before and after applying wash hands with soap and water
- Children under 12 years must ask a doctor

WARNINGS

For external use only

Do not use on large areas of the body or on cut, irritated or swollen skin, on puncture wounds, or for more than one week without consulting a doctor.

INACTIVE INGREDIENT

Benzyl alcohol, carbomer, glycerin, hydrogenated lecithin, isopropyl palmitate, polysorbate 80, triethanolamine, Vitamin E, water

Keep out of reach of children and pets

Stop using and ask a doctor if

- condition worsens
- redness is present
- irritation develops
- symptoms persist for more than 7 days or clear up and occur again within few days
- you experience signs of skin injury such as pain, swelling, or blistering where the product was applied

Questions? 1-800-925-4733

WHEN USING

- Use as directed. read and follow all directions and warnings
- rare cases of serious burns have been reported with products of this type
- do not bandage or apply local heat to the area of use with a medicated patch
- avoiding contact with eyes and mucus membrane
- a transient burning sensation may occur upon application but generally disappears in several days